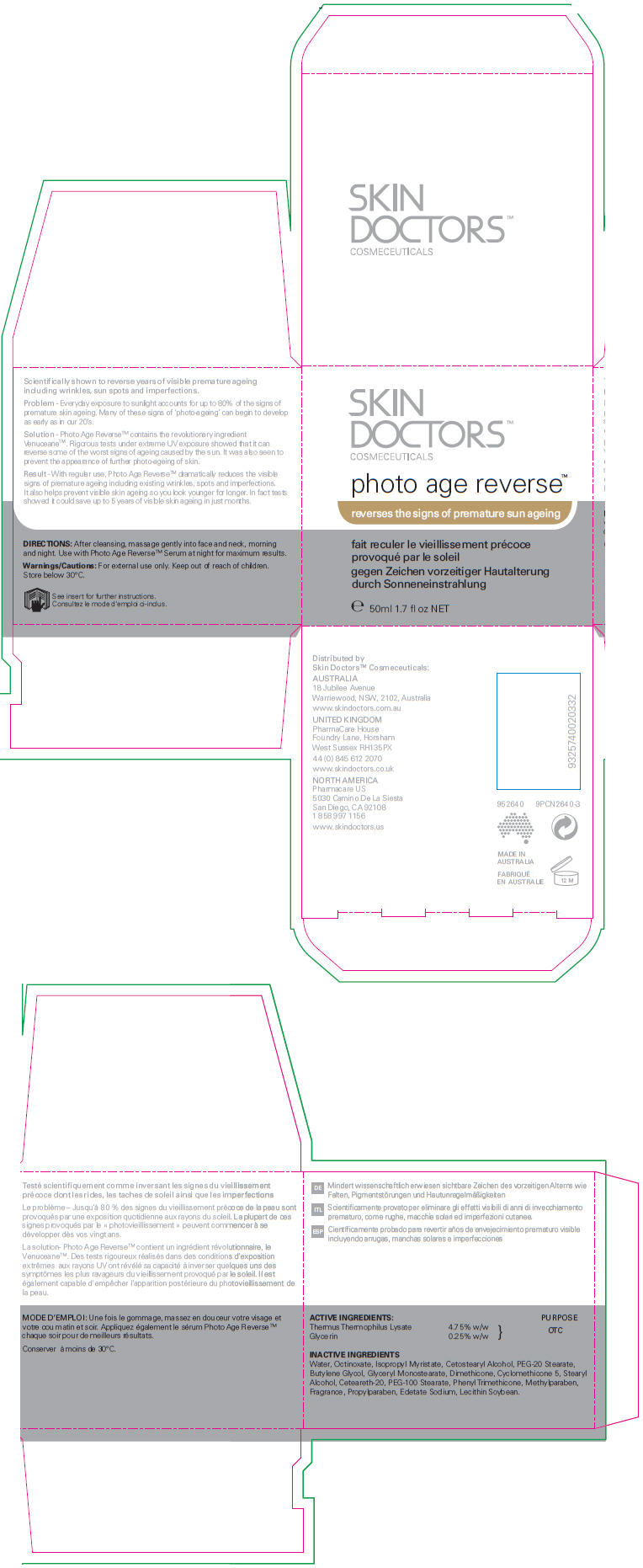 DRUG LABEL: Skin Doctors Photo Age Reverse
NDC: 49203-740 | Form: CREAM
Manufacturer: Cat Media Pty Ltd
Category: otc | Type: HUMAN OTC DRUG LABEL
Date: 20120711

ACTIVE INGREDIENTS: Thermus Thermophilus Lysate 46.1 mg/1 mL; Glycerin 2.4 mg/1 mL
INACTIVE INGREDIENTS: Water; Octinoxate; Isopropyl Myristate; Cetostearyl Alcohol; PEG-20 Stearate; Butylene Glycol; Methylparaben; Propylparaben; Glyceryl Monostearate; Dimethicone 200; Cyclomethicone 5; PEG/PPG-18/18 DIMETHICONE; Stearyl Alcohol; Polyoxyl 20 Cetostearyl Ether; PEG-100 STEARATE; Phenyl Trimethicone; Edetate Disodium; Lecithin, Soybean; Phenoxyethanol; Potassium Sorbate

Skin Doctors™ Photo Age Reverse™ Cream

INDICATIONS AND USAGE

Scientifically shown to reverse years of visible premature ageing including wrinkles, sun spots and imperfections.

Problem - Everyday exposure to sunlight accounts for up to 80% of the signs of premature skin ageing. Many of these signs of 'photo-ageing' can begin to develop as early as in our 20's.

Solution - Photo Age Reverse™ contains the revolutionary ingredient Venuceane™. Rigorous tests under extreme UV exposure showed that it can reverse some of the worst signs of ageing caused by the sun. It was also seen to prevent the appearance of further photo-ageing of skin.

Result - With regular use, Photo Age Reverse™ dramatically reduces the visible signs of premature ageing including existing wrinkles, spots and imperfections. It also helps prevent visible skin ageing so you look younger for longer. In fact tests showed it could save up to 5 years of visible skin ageing in just months.

ACTIVE INGREDIENT

ACTIVE INGREDIENTS: |  | PURPOSE
Thermus Thermophilus Lysate | 4.75% w/w | OTC
Glycerin | 0.25% w/w | OTC

INACTIVE INGREDIENTS

Water, Octinoxate, Isopropyl Myristate, Cetostearyl Alcohol, PEG-20 Stearate, Butylene Glycol, Glyceryl Monostearate, Dimethicone, Cyclomethicone 5, Stearyl Alcohol, Ceteareth-20, PEG-100 Stearate, Phenyl Trimethicone, Methylparaben, Fragrance, Propylparaben, Edetate Sodium, Lecithin Soybean.

DIRECTIONS

After cleansing, massage gently into face and neck, morning and night. Use with Photo Age Reverse™ Serum at night for maximum results.

Warnings/Cautions

For external use only.

Keep out of reach of children.

STORAGE AND HANDLING

Store below 30°C.

Distributed by
Skin Doctors™ Cosmeceuticals

NORTH AMERICA
Pharmacare US
5030 Camino De La Siesta
San Diego, CA 92108

PRINCIPAL DISPLAY PANEL - 50 ml Jar Carton

SKIN
DOCTORS™
COSMECEUTICALS

photo age reverse™

reverses the signs of premature sun ageing

e 50ml 1.7 fl oz NET